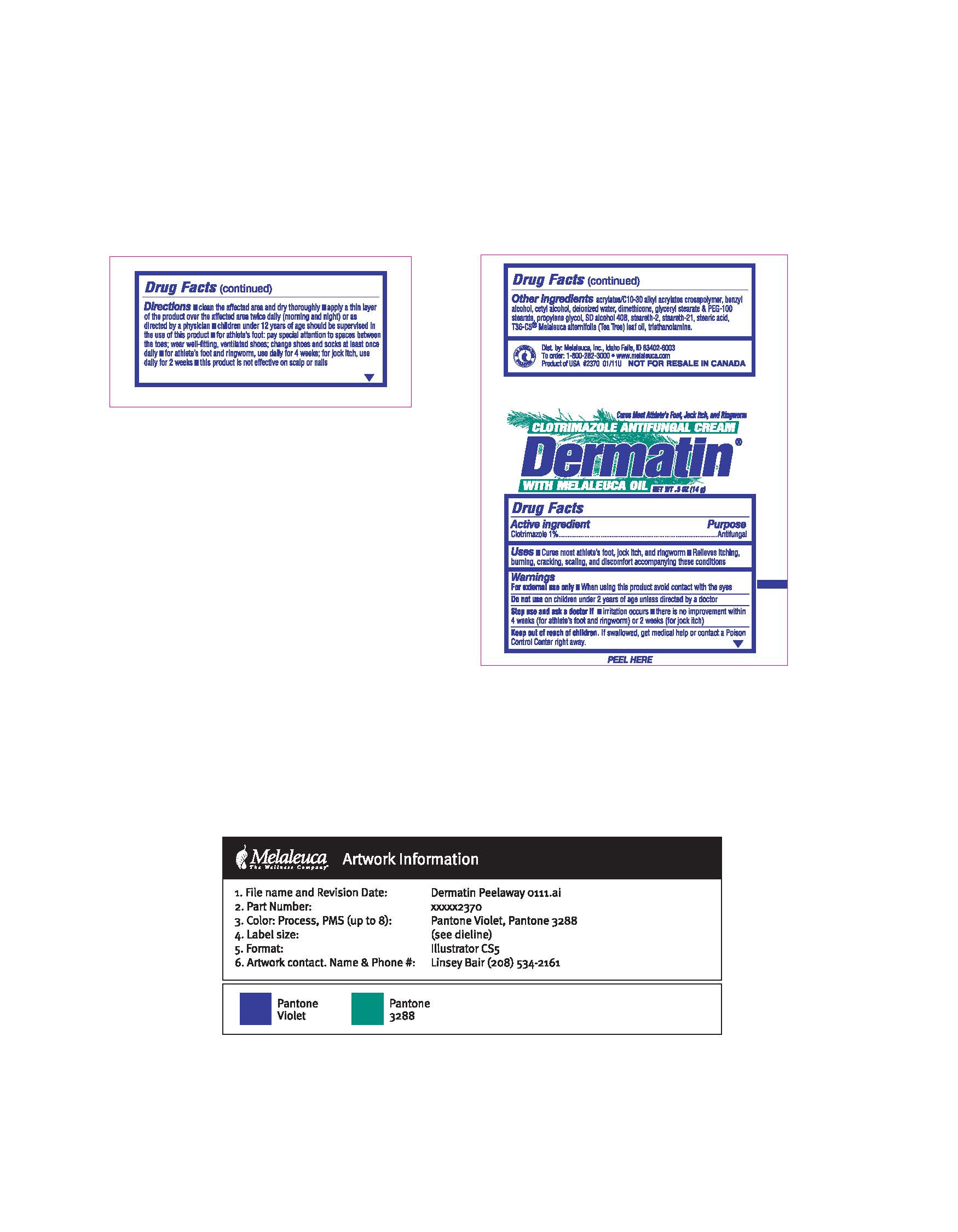 DRUG LABEL: Dermatin
NDC: 54473-096 | Form: CREAM
Manufacturer: Melaleuca, Inc.
Category: otc | Type: HUMAN OTC DRUG LABEL
Date: 20250320

ACTIVE INGREDIENTS: CLOTRIMAZOLE 0.01 g/1 g
INACTIVE INGREDIENTS: CARBOMER COPOLYMER TYPE A (ALLYL PENTAERYTHRITOL CROSSLINKED); ALCOHOL; CETYL ALCOHOL; DIMETHICONE; GLYCERYL STEARATE SE; PEG-100 STEARATE; PROPYLENE GLYCOL; STEARETH-2; STEARETH-21; STEARIC ACID; TEA TREE OIL; WATER; TROLAMINE; BENZYL ALCOHOL

Dermatin Antifungal

Active ingredients
Clotrimazole 1%

Purpose
Antifungal

Uses

- Cures most athlete's foot, jock itch, and ringworm
- Relieves itching, burning, cracking, scaling, and discomfort accompanying these conditions

Warnings
For external use only

- When using this product avoid contact with the eyes

Do not use on children under 2 years of age unless directed by a doctor

Stop use and ask a doctor if

- irritation occurs
- there is no improvement within 4 weeks (for athlete's foot and ringworm) or 2 weeks (for jock itch)

Keep out of reach of children. If swallowed, get medical help or contact a Poison Control Center right away.

Directions

- clean the affected area and dry thoroughly
- apply a thin layer of the product over the affected area twice daily (morning and night) or as directed by a physician
- children under 12 years of age should be supervised in the use of this product
- for athlete's foot: pay special attention to spaces between the toes: wear well-fitting, ventilated shoes: change shoes and socks at least once daily
- for athletes foot and ringworm, use daily for 4 weeks: for jock itch, use daily for 2 weeks
- this product is not effective on scalp or nails

INACTIVE INGREDIENT

Other ingredients Water, T36 C5 Melaleuca Oil, Stearic Acid, Cetyl alcohol, SD Alcohol 40B, Glyceryl Stearate and PEG 100 Stearate, Steareth 21, Propylene Glycol, Dimethicone, Acrylates/C10-30 Alkylacrylates Crosspolymer, Triethanolamine, Steareth 2, Benzyl Alcohol, Methylsothiazolinone, BHT.